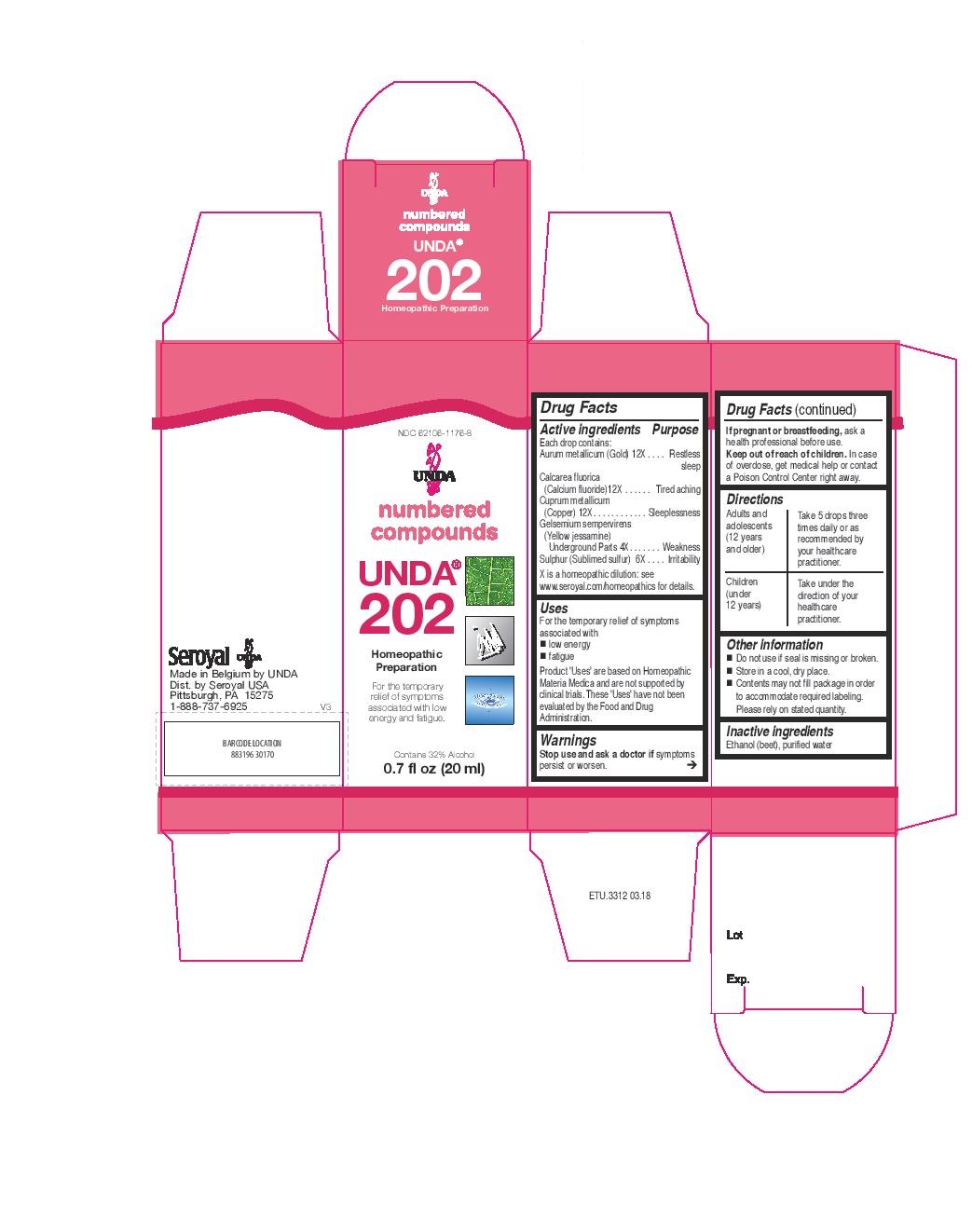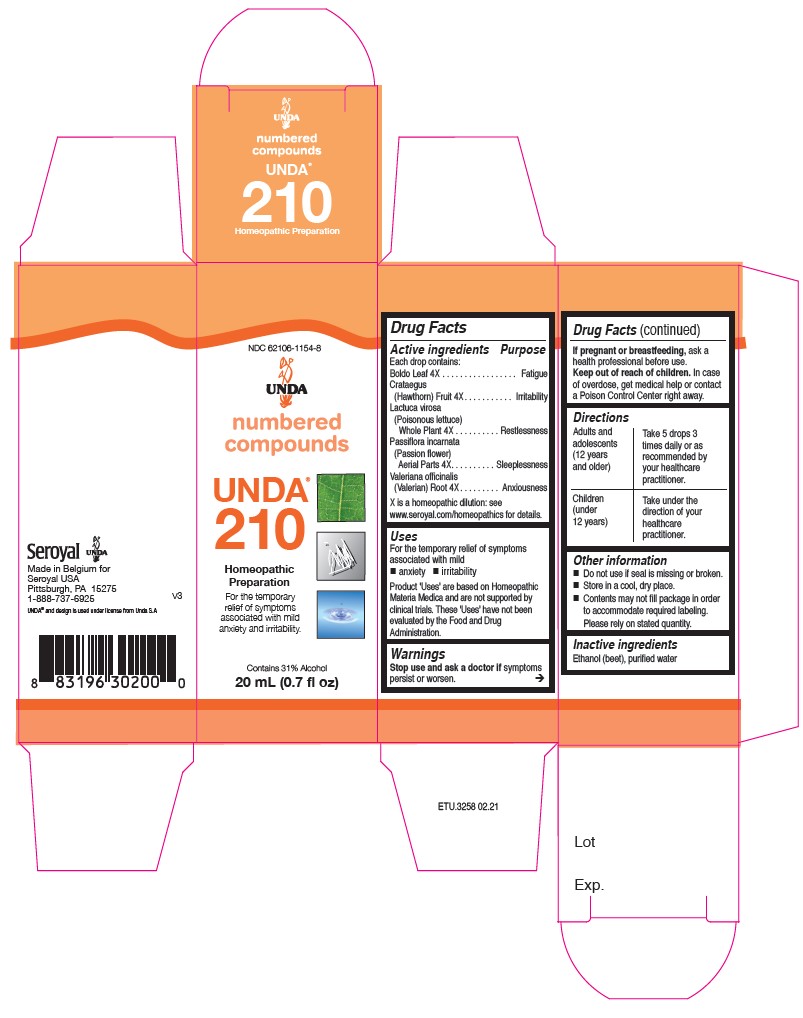 DRUG LABEL: UNDA 210
NDC: 62106-1154 | Form: LIQUID
Manufacturer: Seroyal USA
Category: homeopathic | Type: HUMAN OTC DRUG LABEL
Date: 20210715

ACTIVE INGREDIENTS: PEUMUS BOLDUS LEAF 4 [hp_X]/20 mL; CRATAEGUS FRUIT 4 [hp_X]/20 mL; LACTUCA VIROSA 4 [hp_X]/20 mL; PASSIFLORA INCARNATA FLOWERING TOP 4 [hp_X]/20 mL; VALERIAN 4 [hp_X]/20 mL
INACTIVE INGREDIENTS: ALCOHOL; WATER

UNDA 202 and 210

Active ingredients
Each drop contains:
Aurum metallicum (Gold) 12X
Calcarea fluorica (Calcium fluoride)12X
Cuprum metallicum (Copper) 12X
Gelsemium sempervirens (Yellow jessamine) Underground Parts 4X
Sulphur (Sublimed sulfur) 6X

Uses
For the temporary relief of symptoms associated with
low energy
fatigue

Warnings
Stop use and ask a doctor if symptoms persist or worsen.
If pregnant or breastfeeding, ask a health professional before use.
Keep out of reach of children.
In case of overdose, get medical help or contact a Poison Control Center right away.

Stop use and ask a doctor if symptoms persist or worsen.

PREGNANCY OR BREAST FEEDING

If pregnant or breastfeeding, ask a health professional before use.

Keep out of reach of children.

OVERDOSAGE

In case of overdose, get medical help or contact a Poison Control Center right away.

Inactive ingredients
Ethanol (beet), purified water

Other information
Do not use if seal is missing or broken.

Store in a cool, dry place.

Contents may not fill package in order to accommodate required labeling. Please rely on stated quantity.

Directions
Adults and adolescents (12 years and older): Take 5 drops three times daily or as
recommended by your healthcare practitioner.
Children (under 12 years): Take under the direction of your
healthcare practitioner.

Uses
For the temporary relief of symptoms associated with
low energy
fatigue

Directions
Adults and adolescents (12 years and older): Take 5 drops three times daily or as
recommended by your healthcare practitioner.
Children (under 12 years): Take under the direction of your
healthcare practitioner.

Active ingredients

Each drop contains:

Boldo Leaf 4X
Crataegus (Hawthorn) Fruit 4X
Lactuca virosa (Poisonous lettuce) Whole Plant 4X
Passiflora incarnata (Passion flower) Aerial Parts 4X
Valeriana officinalis (Valerian) Root 4X

Uses
For the temporary relief of symptoms associated with mild anxiety and irritability

Warnings
Stop use and ask a doctor if symptoms persist or worsen.
If pregnant or breastfeeding, ask a health professional before use.
Keep out of reach of children.
In case of overdose, get medical help or contact a Poison Control Center right away.

Stop use and ask a doctor if symptoms persist or worsen.

PREGNANCY OR BREAST FEEDING

If pregnant or breastfeeding, ask a health professional before use.

Keep out of reach of children.

OVERDOSAGE

In case of overdose, get medical help or contact a Poison Control Center right away.

Inactive ingredients
Ethanol (beet), purified water

Other information
Do not use if seal is missing or broken.
Store in a cool, dry place.

Contents may not fill package in order
to accommodate required labeling.
Please rely on stated quantity.

Directions
Adults and adolescents (12 years and older): Take 5 drops three times daily or as
recommended by your healthcare practitioner.
Children (under 12 years): Take under the direction of your
healthcare practitioner.

Uses
For the temporary relief of symptoms associated with mild anxiety and irritability

Directions
Adults and adolescents (12 years and older): Take 5 drops three times daily or as
recommended by your healthcare practitioner.
Children (under 12 years): Take under the direction of your
healthcare practitioner.

PACKAGE LABEL

NDC 62106-1176-8

UNDA
numbered compounds
UNDA 202
Homeopathic Preparation

For the temporary relief of symptoms
associated with low energy and fatigue.
Contains 32% Alcohol
0.7 fl oz (20 mL)

PACKAGE LABEL

NDC 62106-1154-8

UNDA
numbered compounds
UNDA 210
Homeopathic Preparation

For the temporary relief of symptoms
associated with mild anxiety and irritability.
Contains 31% Alcohol
0.7 fl oz (20 ml)